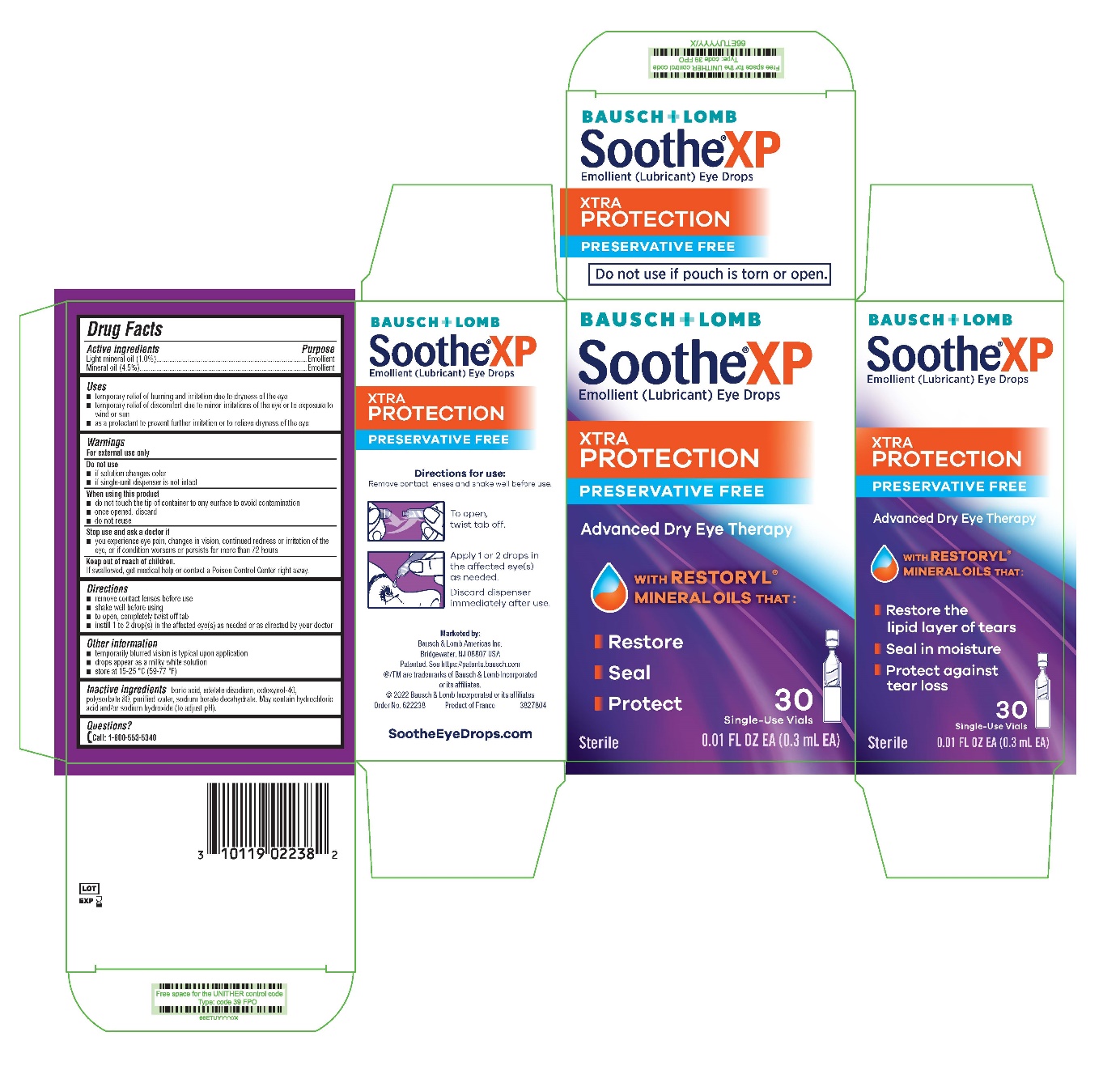 DRUG LABEL: Soothe XP Preservative Free
NDC: 24208-742 | Form: SOLUTION/ DROPS
Manufacturer: Bausch & Lomb Incorporated
Category: otc | Type: HUMAN OTC DRUG LABEL
Date: 20240920

ACTIVE INGREDIENTS: LIGHT MINERAL OIL 10 mg/1 mL; MINERAL OIL 45 mg/1 mL
INACTIVE INGREDIENTS: BORIC ACID; EDETATE DISODIUM; OCTOXYNOL-40; POLYSORBATE 80; WATER; SODIUM BORATE; HYDROCHLORIC ACID; SODIUM HYDROXIDE

Drug Facts

Active ingredients

Light mineral oil (1.0%)

Mineral oil (4.5%)

Purpose

Emollient

Emollient

Uses

- temporary relief of burning and irritation due to dryness of the eye
- temporary relief of discomfort due to minor irritations of the eye or to exposure to wind or sun
- as a protectant to prevent further irritation or to relieve dryness of the eye

Warnings

For external use only

Do not use

- if solution changes color
- if single-unit dispenser is not intact

When using this product

- do not touch the tip of container to any surface to avoid contamination
- once opened, discard
- do not reuse

Stop use and ask a doctor if

- you experience eye pain, changes in vision, continued redness or irritation of the eye, or if condition worsens or persists for more than 72 hours

Keep out of reach of children.

If swallowed, get medical help or contact a Poison Control Center right away.

Directions

- remove contact lenses before use
- shake well before using
- to open, completely twist off tab
- instill 1 to 2 drop(s) in the affected eye(s) as needed or as directed by your doctor

Other information

- temporarily blurred vision is typical upon application
- drops appear as a milky white solution
- store at 15-25 °C (59-77 °F)

Inactive ingredients

boric acid, edetate disodium, octoxynol-40, polysorbate 80, purified water, sodium borate decahydrate. May contain hydrochloric acid and/or sodium hydroxide (to adjust pH).

Questions?

Call: 1-800-553-5340

Marketed by:
Bausch & Lomb Americas Inc.
Bridgewater, NJ 08807 USA
Patented. See https://patents.bausch.com
®/TM are trademarks of Bausch & Lomb Incorporated
or its affiliates.
© 2022 Bausch & Lomb Incorporated or its affiliates
Order No. 622238
Product of France

3827804
SootheEyeDrops.com

Package/Label Principal Display Panel

BAUSCH + LOMB

Soothe®XP

Emollient (Lubricant) Eye Drops

XTRA PROTECTION

Preservative Free

Advanced Dry Eye Therapy

With Restoryl ®

mineral oils that:

• Restore

• Seal

• Protect

30 Single-Use Vials

0.01 FL OZ EA (0.3 mL EA)

Sterile